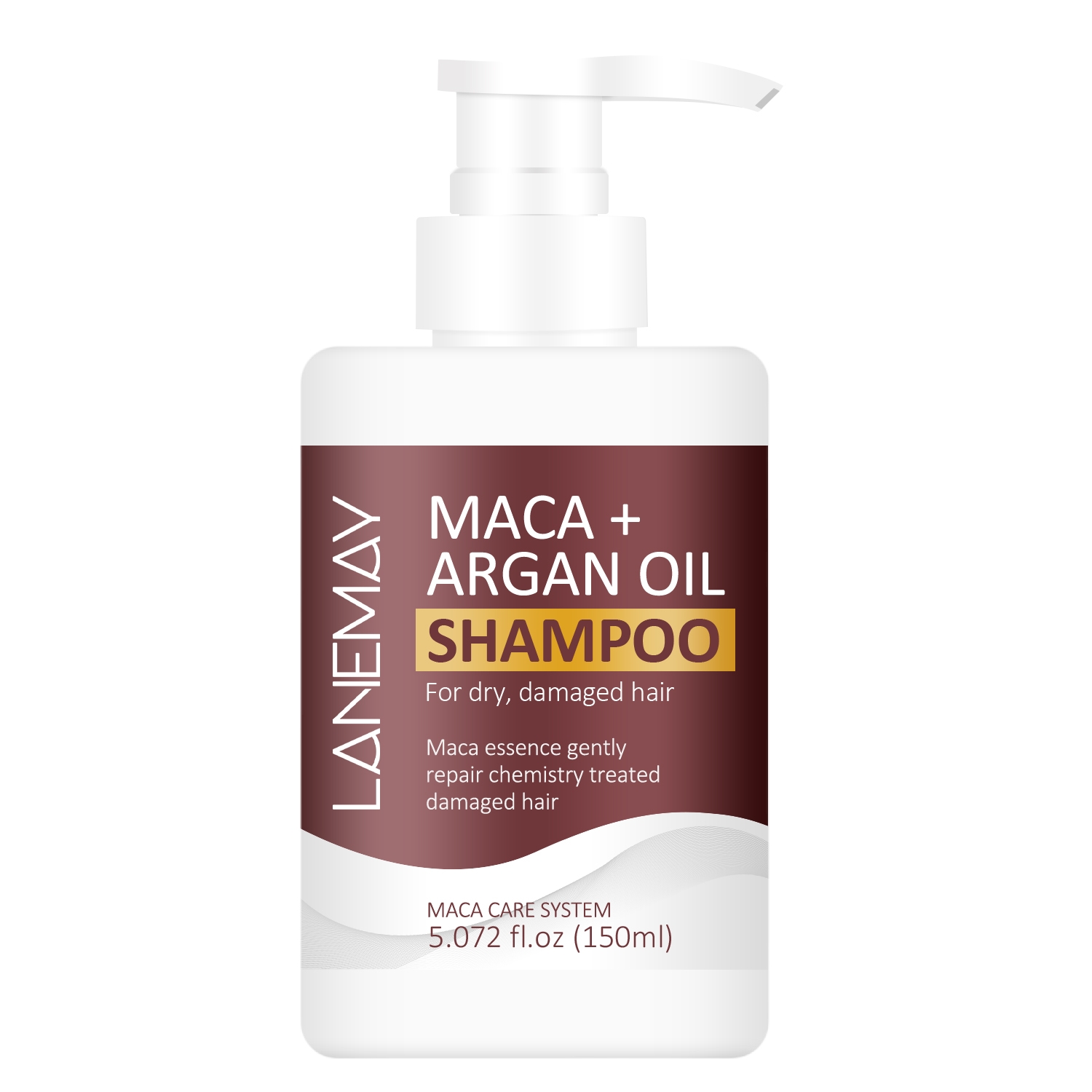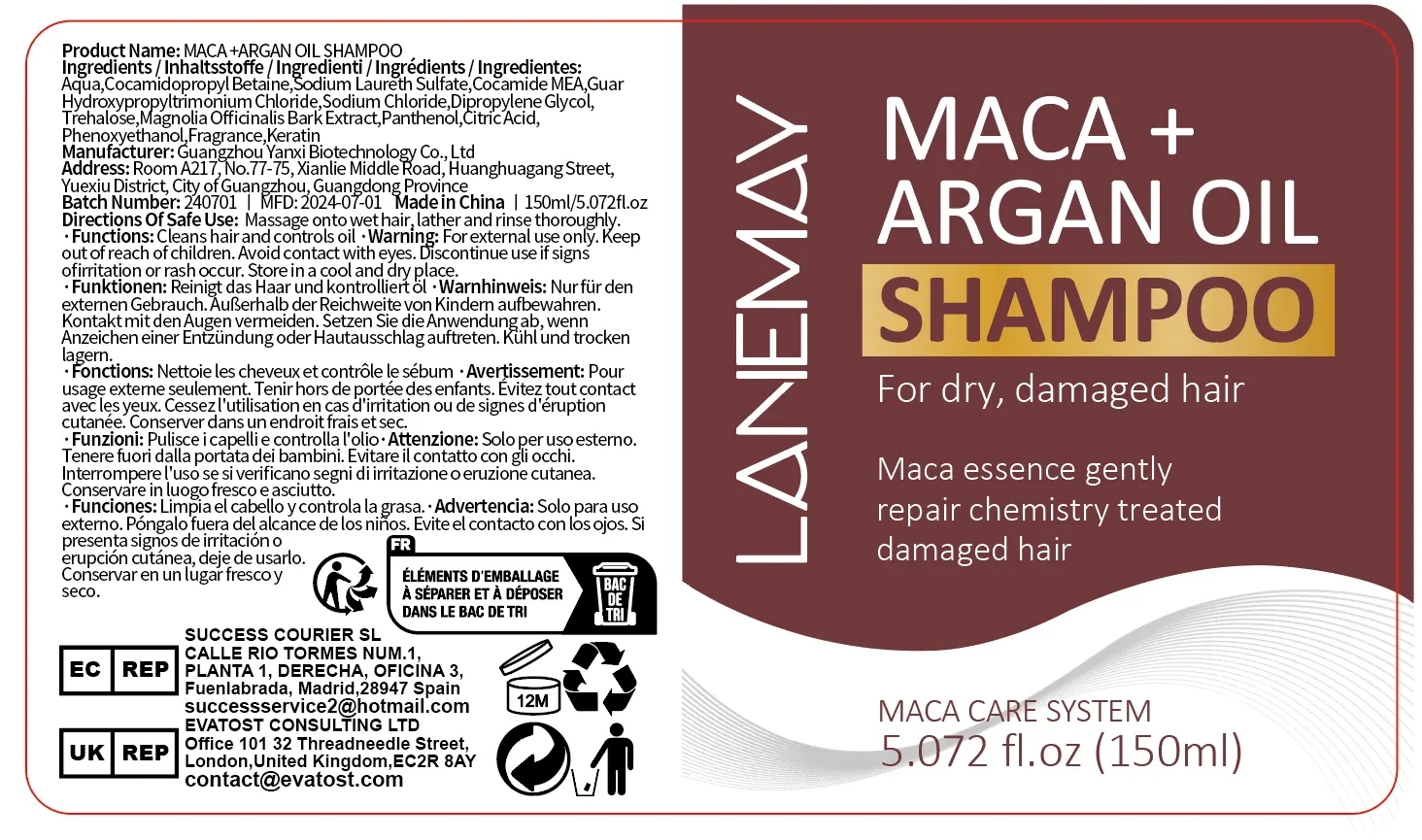 DRUG LABEL: Mava Argan OilShampoo
NDC: 84025-219 | Form: SHAMPOO
Manufacturer: Guangzhou Yanxi Biotechnology Co., Ltd
Category: otc | Type: HUMAN OTC DRUG LABEL
Date: 20241018

ACTIVE INGREDIENTS: DIPROPYLENE GLYCOL 3 mg/100 mL; COCAMIDOPROPYL BETAINE 5 mg/100 mL
INACTIVE INGREDIENTS: WATER

DOSAGE AND ADMINISTRATION

use as a normal hair cream

WARNINGS

keep out of children

INACTIVE INGREDIENT

Aqua

INDICATIONS AND USAGE

for daily hair cleaning

keep out of children

PURPOSE

Make hair fluffy and soft